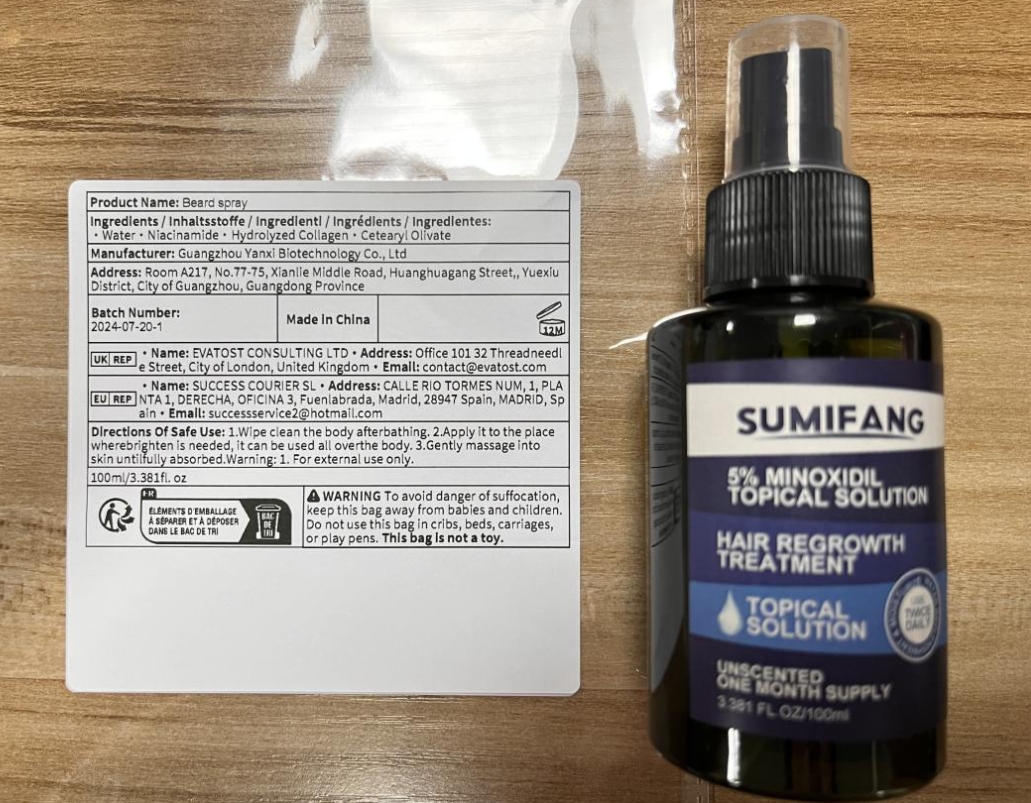 DRUG LABEL: Beardspray
NDC: 84025-085 | Form: SPRAY
Manufacturer: Guangzhou Yanxi Biotechnology Co., Ltd
Category: otc | Type: HUMAN OTC DRUG LABEL
Date: 20240724

ACTIVE INGREDIENTS: NIACINAMIDE 5 mg/100 mL; CETEARYL OLIVATE 3 mg/100 mL
INACTIVE INGREDIENTS: WATER

DOSAGE AND ADMINISTRATION

Spray the product onto the beard after cleaning the face

WARNINGS

keep out of children

INACTIVE INGREDIENT

Aqua

INDICATIONS AND USAGE

Whiskers grow faster

keep out of children

PURPOSE

Delay beard growth